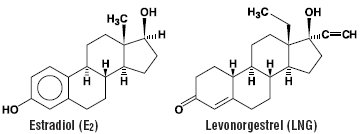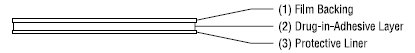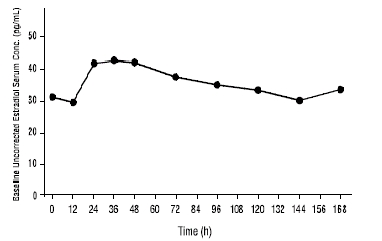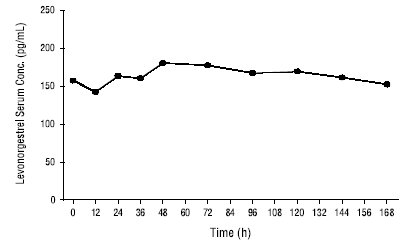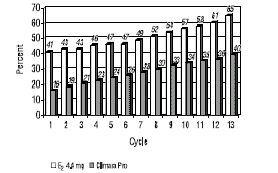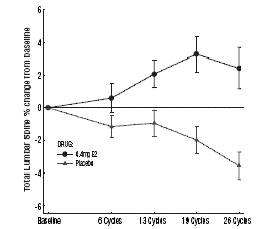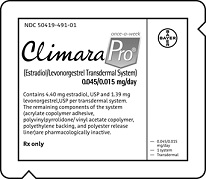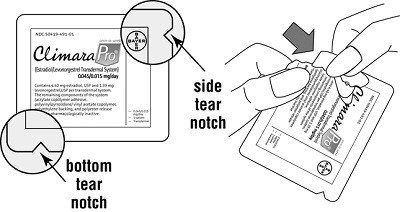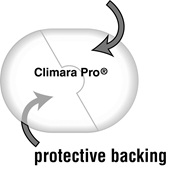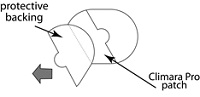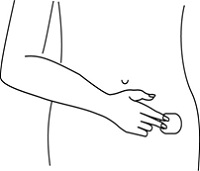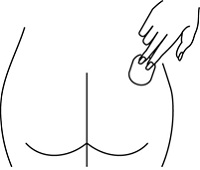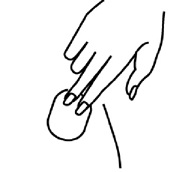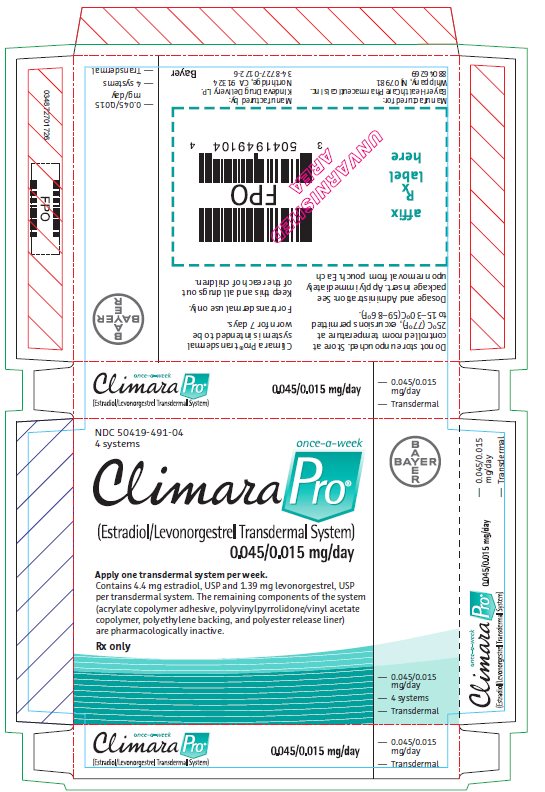 DRUG LABEL: Climara Pro
NDC: 50419-491 | Form: PATCH
Manufacturer: Bayer HealthCare Pharmaceuticals Inc.
Category: prescription | Type: HUMAN PRESCRIPTION DRUG LABEL
Date: 20231206

ACTIVE INGREDIENTS: ESTRADIOL 0.045 mg/1 d; LEVONORGESTREL 0.015 mg/1 d

HIGHLIGHTS OF PRESCRIBING INFORMATION

These highlights do not include all the information needed to use CLIMARA PRO safely and effectively. See full prescribing information for CLIMARA PRO.
Climara Pro® (estradiol/levonorgestrel transdermal system)
Initial U.S. Approval: 1975

RECENT MAJOR CHANGES

Warnings and Precautions (5.2) 12/2023

WARNING: CARDIOVASCULAR DISORDERS, PROBABLE DEMENTIA, BREAST CANCER, and ENDOMETRIAL CANCER

See full prescribing information for complete boxed warning.

Estrogen Plus Progestin Therapy

- The Women’s Health Initiative (WHI) estrogen plus progestin substudy reported increased risks of stroke, deep vein thrombosis (DVT), pulmonary embolism (PE), and myocardial infarction (MI) (5.1)
- The WHI estrogen plus progestin substudy reported increased risks of invasive breast cancer (5.2)
- The WHI Memory Study (WHIMS) estrogen plus progestin ancillary study of WHI reported an increased risk of probable dementia in postmenopausal women 65 years of age and older (5.3)
- Do not use estrogen plus progestogen therapy for the prevention of cardiovascular disease or dementia (5.1, 5.3)

Estrogen-Alone Therapy

- There is an increased risk of endometrial cancer in a woman with a uterus who uses unopposed estrogens (5.2)
- The WHI estrogen-alone substudy reported increased risks of stroke and DVT (5.1)
- The WHIMS estrogen-alone ancillary study of WHI reported an increased risk of probable dementia in postmenopausal women 65 years of age and older (5.3)
- Do not use estrogen-alone therapy for the prevention of cardiovascular disease or dementia (5.1, 5.3)

1 INDICATIONS AND USAGE

Climara Pro is an estrogen plus progestin indicated in a woman with a uterus for:

- Treatment of Moderate to Severe Vasomotor Symptoms due to Menopause (1.1)
- Prevention of Postmenopausal Osteoporosis (1.2)
  Limitations of Use:
  When prescribing solely for the prevention of postmenopausal osteoporosis, first consider the use of non-estrogen medications. Consider estrogen therapy only for women at significant risk of osteoporosis.

2 DOSAGE AND ADMINISTRATION

- Apply Climara Pro 0.045 mg per day/0.015 mg per day once-weekly to the lower abdomen (2.3)

3 DOSAGE FORMS AND STRENGTHS

- Transdermal system 0.045 mg/day estradiol and 0.015 mg/day levonorgestrel (3)

4 CONTRAINDICATIONS

- Undiagnosed abnormal genital bleeding (4, 5.2)
- Breast cancer or a history of breast cancer (4, 5.2)
- Estrogen-dependent neoplasia (4, 5.2)
- Active DVT, PE or a history of these conditions (4, 5.1)
- Active arterial thromboembolic disease (for example, stroke and MI), or a history of these conditions (4, 5.1)
- Known anaphylactic reaction or angioedema or hypersensitivity to Climara Pro (4)
- Hepatic impairment or disease (4, 5.10)
- Protein C, protein S, or antithrombin deficiency, or other thrombophilic disorders (4)

5 WARNINGS AND PRECAUTIONS

- Estrogens increase the risk of gallbladder disease (5.4)
- Discontinue estrogens if severe hypercalcemia, loss of vision, severe hypertriglyceridemia or cholestatic jaundice occurs (5.5, 5.6, 5.9, 5.10)
- Monitor thyroid function in women on thyroid hormone replacement therapy (5.11, 5.18)

6 ADVERSE REACTIONS

- The most common adverse reactions (≥5 percent) with Climara Pro are: application site reaction, vaginal bleeding, breast pain, upper respiratory infection, back pain, depression, pain, headache and flu syndrome. (6.1)

To report SUSPECTED ADVERSE REACTIONS, contact 1-888-84-BAYER (1-888-842-2937) or FDA at 1-800-FDA-1088 or www.fda.gov/medwatch.

7 DRUG INTERACTIONS

- Inducers and/or inhibitors of CYP3A4 may affect estrogen drug metabolism and decrease or increase the estrogen plasma concentration. (7)
- Hydroxylation of levonorgestrel may interact with inhibitors of CYP3A, CYP2E and CYP2C and decrease the therapeutic effects. (7)

FULL PRESCRIBING INFORMATION

WARNING: CARDIOVASCULAR DISORDERS, PROBABLE DEMENTIA, BREAST CANCER, and ENDOMETRIAL CANCER

Estrogen Plus Progestin Therapy

Cardiovascular Disorders and Probable Dementia

The Women's Health Initiative (WHI) estrogen plus progestin substudy reported an increased risk of deep vein thrombosis (DVT), pulmonary embolism (PE), stroke and myocardial infarction (MI) in postmenopausal women (50 to 79 years of age) during 5.6 years of treatment with daily oral conjugated estrogens (CE) [0.625 mg] combined with medroxyprogesterone acetate (MPA) [2.5 mg], relative to placebo [see Warnings and Precautions (5.1), and Clinical Studies (14.5)].

The WHI Memory Study (WHIMS) estrogen plus progestin ancillary study of WHI reported an increased risk of developing probable dementia in postmenopausal women 65 years of age and older during 4 years of treatment with daily CE (0.625 mg) combined with MPA (2.5 mg), relative to placebo. It is unknown whether this finding applies to younger postmenopausal women [see Warnings and Precautions (5.3), Use in Specific Populations (8.5), and Clinical Studies (14.6)].

Do not use estrogen plus progestogen therapy for the prevention of cardiovascular disease or dementia [see Warnings and Precautions (5.1, 5.3), and Clinical Studies (14.5, 14.6)].

Breast Cancer

The WHI estrogen plus progestin substudy demonstrated an increased risk of invasive breast cancer [see Warnings and Precautions (5.2), and Clinical Studies (14.5)].

Only daily oral 0.625 mg CE and MPA were studied in the estrogen plus progestin substudy of the WHI. Therefore, the relevance of the WHI findings regarding adverse cardiovascular events, dementia and breast cancer to lower CE plus other MPA doses, other routes of administration, or other estrogen plus progestogen products is not known. Without such data, it is not possible to definitively exclude these risks or determine the extent of these risks for other products. Discuss with your patient the benefits and risks of estrogen plus progestogen therapy, taking into account her individual risk profile.

Prescribe estrogens with or without progestogens at the lowest effective doses and for the shortest duration consistent with treatment goals and risks for the individual woman.

Estrogen-Alone Therapy

Endometrial Cancer

There is an increased risk of endometrial cancer in a woman with a uterus who uses unopposed estrogens. Adding a progestogen to estrogen therapy has been shown to reduce the risk of endometrial hyperplasia, which may be a precursor to endometrial cancer. Perform adequate diagnostic measures, including directed or random endometrial sampling when indicated rule out malignancy in postmenopausal women with undiagnosed persistent or recurring abnormal genital bleeding [see Warnings and Precautions (5.2)].

Cardiovascular Disorders and Probable Dementia

The WHI estrogen-alone substudy reported increased risks of stroke and DVT in postmenopausal women (50 to 79 years of age) during 7.1 years of treatment with daily oral CE (0.625 mg)-alone, relative to placebo [see Warnings and Precautions (5.1), and Clinical Studies (14.5)].

The WHIMS estrogen-alone ancillary study of WHI reported an increased risk of developing probable dementia in postmenopausal women 65 years of age and older during 5.2 years of treatment with daily CE (0.625 mg)-alone, relative to placebo. It is unknown whether this finding applies to younger postmenopausal women [see Warnings and Precautions (5.3), Use in Specific Populations (8.5), and Clinical Studies (14.6)].

Do not use estrogen-alone therapy for the prevention of cardiovascular disease or dementia [see Warnings and Precautions (5.1, 5.3), and Clinical Studies (14.5, 14.6)].

Only daily oral 0.625 mg CE was studied in the estrogen-alone substudy of the WHI. Therefore, the relevance of the WHI findings regarding adverse cardiovascular events and dementia to lower CE doses, other routes of administration, or other estrogen-alone products is not known. Without such data, it is not possible to definitively exclude these risks or determine the extent of these risks for other products. Discuss with your patient the benefits and risks of estrogen-alone therapy, taking into account her individual risk profile.

Prescribe estrogens with or without progestogens at the lowest effective doses and for the shortest duration consistent with treatment goals and risks for the individual woman.

1 INDICATIONS AND USAGE

Climara Pro is indicated for:

1.2 Prevention of Postmenopausal Osteoporosis

Limitation of Use

When prescribing solely for the prevention of postmenopausal osteoporosis, first consider the use of non-estrogen medications. Consider estrogen therapy only for women at significant risk of osteoporosis.

2 DOSAGE AND ADMINISTRATION

Use estrogen-alone, or in combination with a progestogen, at the lowest effective dose and for the shortest duration consistent with treatment goals and risks for the individual women. Reevaluate postmenopausal women periodically as clinically appropriate to determine if treatment is still necessary.

One Climara Pro transdermal system is available for use.

2.1 Treatment of Moderate to Severe Vasomotor Symptoms due to Menopause

Start therapy with Climara Pro 0.045 mg per day/0.015 mg per day applied to the skin once weekly. Start therapy at the lowest effective dose and the shortest duration consistent with the treatment goals. Attempts to discontinue Climara Pro should be made at 3 to 6 month intervals.

2.2 Prevention of Postmenopausal Osteoporosis

Apply Climara Pro 0.045 mg per day/0.015 mg per day applied to the skin once weekly.

2.3 Application of the Climara Pro Transdermal System

Initiation of Therapy

Women not currently using continuous estrogen-alone therapy or estrogen plus progestogen therapy may start therapy with Climara Pro at any time. However, women currently using continuous estrogen-alone therapy or estrogen plus progestogen therapy should complete the current cycle of therapy before initiating Climara Pro therapy. Women often experience withdrawal bleeding at the completion of the cycle. The first day of this bleeding would be an appropriate time to begin Climara Pro therapy.

Site Selection

- Place the adhesive side of Climara Pro on a smooth (fold free), clean, dry area of the skin on the lower abdomen or the upper quadrant of the buttock.
- Do not apply Climara Pro to or near the breasts.
- Select an area selected that is not oily (which can impair adherence of the system), damaged, or irritated.
- Avoid the waistline; tight clothing may rub Climara Pro off or modify drug delivery.
- Avoid application to areas where sitting would dislodge Climara Pro.
- Rotate the sites of application, with an interval of at least 1-week allowed between applications to the same site.

Application

- Apply Climara Pro immediately after opening the pouch and removing the protective lining.
- Press Climara Pro firmly in place with the fingers for at least 10 seconds, making sure there is good contact, especially around the edges.
- If the system lifts, apply pressure to maintain adhesion.
- In the event that a system should fall off, reapply the same system to another area of the lower abdomen. If the system cannot be reapplied, a new system may be applied, in which case, the original treatment schedule should be continued.
- Only one system should be worn at any one time during 7-day dosing interval.
- Do not expose the applied transdermal system to the sun for prolonged periods of time.
- Swimming, bathing, or using a sauna while using Climara Pro has not been studied, and these activities may decrease the adhesion of the system and the delivery of the estrogen and progestin.

2.4 Removal of the Climara Pro Transdermal System

- Remove Climara Pro carefully and slowly to avoid irritation of the skin.
- If any adhesive remain on the skin after removal of Climara Pro, allow the area to dry for 15 minutes and then gently rub the area with an oil-based cream or lotion should remove the adhesive residue.
- Used patches still contain some active hormones. Carefully fold each patch in half so that it sticks to itself before throwing it away.

3 DOSAGE FORMS AND STRENGTHS

Climara Pro (estradiol/levonorgestrel transdermal system) 0.045 mg/day estradiol and 0.015 mg/day levonorgestrel – each 22 cm^2 system contains 4.4 mg of estradiol and 1.39 mg of levonorgestrel.

4 CONTRAINDICATIONS

Climara Pro is contraindicated in women with any of the following conditions:

- Undiagnosed abnormal genital bleeding [see Warnings and Precautions (5.2)]
- Breast cancer or history of breast cancer [see Warnings and Precautions (5.2)]
- Estrogen-dependent neoplasia [see Warnings and Precautions (5.2)]
- Active DVT, PE or a history of these conditions [see Warnings and Precautions (5.1)]
- Active arterial thromboembolic disease (for example, stroke or MI), or a history of these conditions [ see Warnings and Precautions (5.1)]
- Known anaphylactic reaction, or angioedema, or hypersensitivity to Climara Pro
- Hepatic impairment or disease
- Protein C, protein S, or antithrombin deficiency, or other thrombophilic disorders

5 WARNINGS AND PRECAUTIONS

5.1 Cardiovascular Disorders

Increased risks of PE, DVT, stroke and MI are reported with estrogen plus progestin therapy. Increased risks of stroke and DVT are reported with estrogen-alone therapy. Immediately discontinue estrogen with or without progestogen therapy if any of these occur or are suspected.

Manage appropriately any risk factors for arterial vascular disease (for example, hypertension, diabetes mellitus, tobacco use, hypercholesterolemia, and obesity) and/or venous thromboembolism (VTE) (for example, personal history or family history of VTE, obesity, and systemic lupus erythematosus).

Stroke

The WHI estrogen plus progestin substudy reported a statistically significant increased risk of stroke in women 50 to 79 years of age receiving daily CE (0.625 mg) plus MPA (2.5 mg) compared to women in the same age group receiving placebo (33 versus 25 strokes per 10,000 women-years, respectively) [see Clinical Studies (14.5)]. The increase in risk was demonstrated after the first year and persisted.^1 Immediately discontinue estrogen plus progestogen therapy if a stroke occurs or is suspected.

The WHI estrogen-alone substudy, reported a statistically significant increased risk of stroke in women 50 to 79 years of age receiving daily CE (0.625 mg)-alone compared to women in the same age group receiving placebo (45 versus 33 strokes per 10,000 women-years, respectively). The increase in risk was demonstrated in year 1 and persisted [see Clinical Studies (14.5)]. Immediately discontinue estrogen-alone therapy if a stroke occurs or is suspected.

Subgroup analyses of women 50 to 59 years of age suggest no increased risk of stroke for those women receiving CE (0.625 mg)-alone versus those receiving placebo (18 versus 21 per 10,000 women-years).^1

Coronary Heart Disease

The WHI estrogen plus progestin substudy reported an increased risk (not statistically significant) of coronary heart disease (CHD) events (defined as nonfatal MI, silent MI, or CHD death) in women receiving daily CE (0.625 mg) plus MPA (2.5 mg) compared to women receiving placebo (41 versus 34 per 10,000 women-years).^1 An increase in relative risk was demonstrated in year 1, and a trend toward decreasing relative risk was reported in years 2 through 5 [see Clinical Studies (14.5)].

The WHI estrogen-alone substudy reported no overall effect on CHD events in women receiving estrogen-alone compared to placebo^2 [see Clinical Studies (14.5].

Subgroup analyses of women 50 to 59 years of age, who were less than 10 years since menopause, suggest a reduction (not statistically significant) of CHD events in those women receiving CE (0.625 mg)-alone compared to placebo (8 versus 16 per 10,000 women-years).^1

In postmenopausal women with documented heart disease (n = 2,763), average 66.7 years of age, in a controlled clinical trial of secondary prevention of cardiovascular disease (Heart and Estrogen/Progestin Replacement Study; HERS), treatment with daily CE (0.625 mg) plus MPA (2.5 mg) demonstrated no cardiovascular benefit. During an average follow-up of 4.1 years, treatment with CE plus MPA did not reduce the overall rate of CHD events in postmenopausal women with established CHD. There were more CHD events in the CE plus MPA-treated group than in the placebo group in year 1, but not during the subsequent years. Two thousand three hundred twenty-one (2,321) women from the original HERS trial agreed to participate in an open label extension of HERS, HERS II. Average follow-up in HERS II was an additional 2.7 years, for a total of 6.8 years overall. Rates of CHD events were comparable among women in the CE plus MPA group and the placebo group in HERS, HERS II, and overall.

Venous Thromboembolism

The WHI estrogen plus progestin substudy reported a statistically significant 2-fold greater rate of VTE (DVT and PE) in women receiving daily CE (0.625 mg) plus MPA (2.5 mg) compared to women receiving placebo (35 versus 17 per 10,000 women-years). Statistically significant increases in risk for both DVT (26 versus 13 per 10,000 women-years) and PE (18 versus 8 per 10,000 women-years) were also demonstrated. The increase in VTE risk was demonstrated during the first year and persisted^3 [see Clinical Studies (14.5)]. Immediately discontinue estrogen plus progestogen therapy if a VTE occurs or is suspected.

In the WHI estrogen-alone substudy, the risk of VTE was increased for women receiving daily CE (0.625 mg)-alone compared to placebo (30 versus 22 per 10,000 women-years), although only the increased risk of DVT reached statistical significance (23 versus 15 per 10,000 women-years). The increase in VTE risk was demonstrated during the first 2 years^4 [see Clinical Studies (14.5)]. Immediately discontinue estrogen-alone therapy if a VTE occurs or is suspected.

If feasible, discontinue estrogens at least 4 to 6 weeks before surgery of the type associated with an increased risk of thromboembolism, or during periods of prolonged immobilization.

5.2 Malignant Neoplasms

Breast Cancer

After a mean follow-up of 5.6 years, the WHI substudy of daily CE (0.625 mg) plus MPA (2.5 mg) reported an increased risk of invasive breast cancer in women who took daily CE plus MPA compared to placebo.

In this substudy, prior use of estrogen-alone or estrogen plus progestin therapy was reported by 26 percent of the women. The relative risk of invasive breast cancer was 1.24, and the absolute risk was 41 versus 33 cases per 10,000 women-years, for CE plus MPA compared with placebo. Among women who reported prior use of hormone therapy, the relative risk of invasive breast cancer was 1.86, and the absolute risk was 46 versus 25 cases per 10,000 women-years, for CE plus MPA compared with placebo. Among women who reported no prior use of hormone therapy, the relative risk of invasive breast cancer was 1.09, and the absolute risk was 40 versus 36 cases per 10,000 women-years for CE plus MPA compared with placebo. In the same substudy, invasive breast cancers were larger, were more likely to be node positive, and were diagnosed at a more advanced stage in the CE (0.625 mg) plus MPA (2.5 mg) group compared with the placebo group. Metastatic disease was rare with no apparent difference between the two groups. Other prognostic factors such as histologic subtype, grade and hormone receptor status did not differ between the groups5 [see Clinical Studies (14.5)].

The WHI substudy of daily CE (0.625 mg)-alone provided information about breast cancer in estrogen-alone users. In the WHI estrogen-alone substudy, after an average follow-up of 7.1 years, daily CE-alone was not associated with an increased risk of invasive breast cancer [relative risk (RR) 0.80] 6 [see Clinical Studies (14.5)].

Consistent with the WHI clinical trials, observational studies have also reported an increased risk of breast cancer with estrogen plus progestin therapy, and a smaller increase in the risk for breast cancer with estrogen-alone therapy, after several years of use. One large meta-analysis of prospective cohort studies reported increased risks that were dependent upon duration of use and could last up to >10 years after discontinuation of estrogen plus progestin therapy and estrogen-alone therapy. Extension of the WHI trials also demonstrated increased breast cancer risk associated with estrogen plus progestin therapy. Observational studies also suggest that the risk of breast cancer was greater, and became apparent earlier, with estrogen plus progestin therapy as compared to estrogen-alone therapy. These studies have not generally found significant variation in the risk of breast cancer among different estrogen plus progestin combinations, doses, or routes of administration.

The use of estrogen-alone and estrogen plus progestin has been reported to result in an increase in abnormal mammograms requiring further evaluation.

All women should receive yearly breast examinations by a healthcare provider and perform monthly breast self-examinations. In addition, mammography examinations should be scheduled based on patient age, risk factors, and prior mammogram results.

Endometrial Cancer

An increased risk of endometrial cancer has been reported with the use of unopposed estrogen therapy in a woman with a uterus. The reported endometrial cancer risk among unopposed estrogen users is about 2 to 12 times greater than in nonusers, and appears dependent on duration of treatment and on estrogen dose. Most studies show no significant increased risk associated with use of estrogens for less than 1 year. The greatest risk appears associated with prolonged use, with increased risks of 15- to 24-fold for 5 to 10 years or more. This risk has been shown to persist for at least 8 to 15 years after estrogen therapy is discontinued.

Clinical surveillance of all women using estrogen-alone or estrogen plus progestogen therapy is important. Perform adequate diagnostic measures, including directed or random endometrial sampling when indicated, to rule out malignancy in postmenopausal women with undiagnosed persistent or recurring abnormal genital bleeding with unknown etiology.

There is no evidence that the use of natural estrogens results in a different endometrial risk profile than synthetic estrogens of equivalent estrogen dose. Adding a progestogen to estrogen therapy in postmenopausal women has been shown to reduce the risk of endometrial hyperplasia, which may be a precursor to endometrial cancer.

Ovarian Cancer

The CE plus MPA substudy of WHI reported that estrogen plus progestin increased the risk of ovarian cancer. After an average follow-up of 5.6 years, the relative risk for ovarian cancer for CE plus MPA versus placebo was 1.58 (95 percent CI, 0.77-3.24), but it was not statistically significant. The absolute risk for CE plus MPA versus placebo was 4 versus 3 cases per 10,000 women-years.^7

A meta-analysis of 17 prospective and 35 retrospective epidemiology studies found that women who used hormonal therapy for menopausal symptoms had an increased risk for ovarian cancer. The primary analysis, using case-control comparisons, included 12,110 cancer cases from the 17 prospective studies. The relative risks associated with current use of hormonal therapy was 1.41 (95% confidence interval [CI] 1.32 to 1.50); there was no difference in the risk estimates by duration of the exposure (less than 5 years [median of 3 years] vs. greater than 5 years [median of 10 years] of use before the cancer diagnosis). The relative risk associated with combined current and recent use (discontinued use within 5 years before cancer diagnosis) was 1.37 (95% CI 1.27 to 1.48), and the elevated risk was significant for both estrogen-alone and estrogen plus progestin products. The exact duration of hormone therapy use associated with an increased risk of ovarian cancer, however, is unknown.

5.3 Probable Dementia

In the WHI Memory Study (WHIMS) estrogen plus progestin ancillary study of WHI, a population of 4,532 postmenopausal women 65 to 79 years of age was randomized to daily CE (0.625 mg) plus MPA (2.5 mg) or placebo.

After an average follow-up of 4 years, 40 women in the CE plus MPA group and 21 women in the placebo group were diagnosed with probable dementia. The relative risk of probable dementia for CE plus MPA versus placebo was 2.05 (95 percent CI, 1.21-3.48). The absolute risk of probable dementia for CE plus MPA versus placebo was 45 versus 22 cases per 10,000 women-years^8 [see Use in Specific Populations (8.5), and Clinical Studies (14.6)].

In the WHIMS estrogen-alone ancillary study of WHI, a population of 2,947 hysterectomized women 65 to 79 years of age was randomized to daily CE (0.625 mg)-alone or placebo.

After an average follow-up of 5.2 years, 28 women in the estrogen-alone group and 19 women in the placebo group were diagnosed with probable dementia. The relative risk of probable dementia for CE-alone versus placebo was 1.49 (95 percent CI, 0.83-2.66). The absolute risk of probable dementia for CE-alone versus placebo was 37 versus 25 cases per 10,000 women-years^8 [see Use in Specific Populations (8.5), and Clinical Studies (14.6)].

When data from the two populations in the WHIMS estrogen-alone and estrogen plus progestin ancillary studies were pooled as planned in the WHIMS protocol, the reported overall relative risk for probable dementia was 1.76 (95 percent CI, 1.19-2.60). Since both ancillary studies were conducted in women 65 to 79 years of age, it is unknown whether these findings apply to younger postmenopausal women^8 [see Use in Specific Populations (8.5), and Clinical Studies (14.6)].

5.4 Gallbladder Disease

A 2- to 4-fold increase in the risk of gallbladder disease requiring surgery in postmenopausal women receiving estrogens has been reported.

5.5 Hypercalcemia

Estrogen administration may lead to severe hypercalcemia in women with breast cancer and bone metastases. Discontinue estrogens, including Climara Pro if hypercalcemia occurs, and take appropriate measures to reduce the serum calcium level.

5.6 Visual Abnormalities

Retinal vascular thrombosis has been reported in women receiving estrogens. Discontinue Climara Pro pending examination if there is sudden partial or complete loss of vision, or a sudden onset of proptosis, diplopia, or migraine. Permanently discontinue estrogens, including Climara Pro, if examination reveals papilledema or retinal vascular lesions.

5.7 Addition of a Progestogen When a Woman Has Not Had a Hysterectomy

Studies of the addition of a progestogen for 10 or more days of a cycle of estrogen administration, or daily with estrogen in a continuous regimen, have reported a lowered incidence of endometrial hyperplasia than would be induced by estrogen treatment alone. Endometrial hyperplasia may be a precursor to endometrial cancer.

There are, however, possible risks that may be associated with the use of progestogens with estrogens compared to estrogen-alone regimens. These include an increased risk of breast cancer.

5.8 Elevated Blood Pressure

In a small number of case reports, substantial increases in blood pressure have been attributed to idiosyncratic reactions to estrogens. In a large, randomized, placebo-controlled clinical trial, a generalized effect of estrogens on blood pressure was not seen.

5.9 Exacerbation of Hypertriglyceridemia

In women with pre-existing hypertriglyceridemia, estrogen therapy may be associated with elevations of plasma triglycerides leading to pancreatitis. Discontinue Climara Pro if pancreatitis occurs.

5.10 Hepatic Impairment and/or Past History of Cholestatic Jaundice

Estrogens may be poorly metabolized in women with hepatic impairment. Exercise caution in any woman with a history of cholestatic jaundice associated with past estrogen use or with pregnancy. In the case of recurrence of cholestatic jaundice, discontinue Climara Pro.

5.11 Exacerbation of Hypothyroidism

Estrogen administration leads to increased thyroid-binding globulin (TBG) levels. Women with normal thyroid function can compensate for the increased TBG by making more thyroid hormone, thus maintaining free T4 and T3 serum concentrations in the normal range. Women dependent on thyroid hormone replacement therapy who are also receiving estrogens may require increased doses of their thyroid replacement therapy. Monitor thyroid function in these women during treatment with Climara Pro to maintain their free thyroid hormone levels in an acceptable range.

5.12 Fluid Retention

Estrogens plus progestogens may cause some degree of fluid retention. Monitor any woman with a condition(s) that might predispose her to fluid retention, such as a cardiac or renal impairment. Discontinue estrogens plus progestogens therapy, including Climara Pro, with evidence of medically concerning fluid retention.

5.13 Hypocalcemia

Estrogen-induced hypocalcemia may occur in women with hypoparathyroidism. Consider whether the benefits of estrogen therapy, including Climara Pro, outweigh the risks in such women.

5.14 Exacerbation of Endometriosis

A few cases of malignant transformation of residual endometrial implants have been reported in women treated post-hysterectomy with estrogen-alone therapy.

5.15 Hereditary Angioedema

Exogenous estrogens may exacerbate symptoms of angioedema in women with hereditary angioedema. Consider whether the benefits of estrogen therapy, including Climara Pro, outweigh the risks in such women.

5.16 Exacerbation of Other Conditions

Estrogen therapy, including Climara Pro, may cause an exacerbation of asthma, diabetes mellitus, epilepsy, migraine, porphyria, systemic lupus erythematosus, and hepatic hemangiomas. Consider whether the benefits of estrogen therapy outweigh the risks in women with these conditions.

5.17 Laboratory Tests

Serum follicle stimulating hormone (FSH) and estradiol levels have not been shown to be useful in the management of postmenopausal women with moderate to severe vasomotor symptoms.

5.18 Drug-Laboratory Test Interactions

Accelerated prothrombin time, partial thromboplastin time, and platelet aggregation time; increased platelet count; increased factors II, VII antigen, VIII antigen, VIII coagulant activity, IX, X, XII, VII-X complex, II-VII-X complex, and beta-thromboglobulin; decreased levels of antifactor Xa and antithrombin III, decreased antithrombin III activity; increased levels of fibrinogen and fibrinogen activity; increased plasminogen antigen and activity.

Increased TBG levels leading to increased circulating total thyroid hormone, as measured by protein-bound iodine (PBI), T4 levels (by column or by radioimmunoassay) or T3 levels by radioimmunoassay. T3 resin uptake is decreased, reflecting the elevated TBG. Free T4 and free T3 concentrations are unaltered. Women on thyroid replacement therapy may require higher doses of thyroid hormone.

Other binding proteins may be elevated in serum, for example, corticosteroid binding globulin (CBG), sex hormone-binding globulin (SHBG), leading to increased total circulating corticosteroids and sex steroids, respectively. Free hormone concentrations, such as testosterone and estradiol, may be decreased. Other plasma proteins may be increased (angiotensinogen/renin substrate, alpha-l-antitrypsin, ceruloplasmin).

Increased plasma high-density lipoprotein (HDL) and HDL2 cholesterol subfraction concentrations, reduced low-density lipoprotein (LDL) cholesterol concentration, and in oral formulations increased triglycerides levels.

Impaired glucose tolerance.

6 ADVERSE REACTIONS

The following serious adverse reactions are discussed elsewhere in the labeling:

- Cardiovascular Disorders [see Boxed Warning, Warnings and Precautions (5.1)]
- Malignant Neoplasms [see Boxed Warning, Warnings and Precautions (5.2)]

6.1 Clinical Trials Experience

Because clinical trials are conducted under widely varying conditions, adverse reaction rates observed in the clinical trials of a drug cannot be directly compared to rates in the clinical trials of another drug and may not reflect the rates observed in practice.

The data described below is from a one-year, prospective, multicenter, double blind, double dummy, randomized, controlled trial investigating the effect of three different dosage combinations of E2/LNG versus E2 alone on the development of endometrial hyperplasia. All women were postmenopausal, had a serum estradiol level of less than 20 pg/mL, and the sample included both symptomatic and asymptomatic women. The data below includes all adverse reactions reported at a frequency of >3% in the E2/LNG 0.045 / 0.015 group (the approved dosage for Climara Pro, N=212) and the E2 alone group (N=204).

Table 1: All Treatment Emergent Reactions Regardless of Relationship Reported at a Frequency of >3% with Climara Pro in the 1-year Endometrial Hyperplasia Study
Body System; Adverse Reaction | Climara Pro 0.045 / 0.015 | E2
Body System; Adverse Reaction | N [N = total number of subjects in a treatment group; n = number of subjects with event.] = 212 | N = 204
Body as a Whole
Abdominal pain | 9 (4.2) | 11 (5.4)
Accidental injury | 7 (3.3) | 6 (2.9)
Back pain | 13 (6.1) | 12 (5.9)
Flu syndrome | 10 (4.7) | 13 (6.4)
Infection | 7 (3.3) | 10 (4.9)
Pain | 11 (5.2) | 13 (6.4)
Cardiovascular System
Hypertension | 7 (3.3) | 9 (4.4)
Digestive System
Flatulence | 8 (3.8) | 11 (5.4)
Metabolic and Nutritional
Edema | 8 (3.8) | 5 (2.5)
Weight gain | 6 (2.8) | 10 (4.9)
Musculoskeletal System
Arthralgia | 9 (4.2) | 10 (4.9)
Nervous System
Depression | 12 (5.7) | 7 (3.4)
Headache | 11 (5.2) | 14 (6.9)
Respiratory System
Bronchitis | 9 (4.2) | 7 (3.4)
Sinusitis | 8 (3.8) | 12 (5.9)
Upper respiratory infection | 28 (13.2) | 26 (12.7)
Skin and Appendages
Application site reaction | 86 (40.6) | 69 (33.8)
Breast pain | 40 (18.9) | 20 (9.8)
Rash | 5 (2.4) | 10 (4.9)
Urogenital System
Urinary Tract Infection | 7 (3.3) | 8 (3.9)
Vaginal Bleeding | 78 (36.8) | 44 (21.6)
Vaginitis | 4 (1.9) | 6 (2.9)

Irritation potential of Climara Pro was assessed in a 3-week irritation study. The study compared the irritation of a Climara Pro placebo patch (22 cm^2) to a placebo (25 cm^2). Visual assessments of irritation were made on Day 7 of each wear period, approximately 30 minutes after patch removal using a 7-point scale (0 = no evidence of irritation; 1 = minimal erythema, barely perceptible; 2 = definite erythema, readily visible, or minimal edema, or minimal papular response; 3–7 = erythema and papules, edema, vesicles, strong extensive reaction).

The mean irritation scores were 0.13 (week 1), 0.12 (week 2), and 0.06 (week 3) for the Climara Pro. The mean scores for the placebo group were 0.2 (week 1), 0.26 (week 2), 0.12 (week 3). There were no irritation scores greater than 2 at any timepoint in any woman.

In controlled clinical trials, withdrawals due to application site reactions occurred in 6 (2.1 percent) of women in the 12-week symptom study and in 71 (8.5 percent) of subjects in the 1-year endometrial protection study.

6.2 Postmarketing Experience

The following adverse reactions have been identified during post-approval use of Climara Pro. Because these reactions are reported voluntarily from a population of uncertain size, it is not always possible to reliably estimate their frequency or establish a causal relationship to drug exposure.

Genitourinary System

Changes in bleeding patterns

Gastrointestinal

Abdominal distension,* abdominal pain,* nausea

Skin

Alopecia, night sweats, pruritus,* Rash,* hot flush*

Central Nervous System

Dizziness, headache, insomnia

Miscellaneous

Application site reaction,* weight increased, anaphylactic reaction

* Combined two or more similar ARs

7 DRUG INTERACTIONS

In vitro and in vivo studies have shown that estrogens are metabolized partially by cytochrome P450 3A4 (CYP3A4). Therefore, inducers or inhibitors of CYP3A4 may affect estrogen drug metabolism. Inducers of CYP3A4 such as St. John's wort (Hypericum perforatum) preparations, phenobarbital, carbamazepine, and rifampin may reduce plasma concentrations of estrogens, possibly resulting in a decrease in therapeutic effects and/or changes in the uterine bleeding profile. Inhibitors of CYP3A4 such as erythromycin, clarithromycin, ketoconazole, itraconazole, ritonavir and grapefruit juice may increase plasma concentrations of estrogens and may result in side effects.

Hydroxylation of levonorgestrel is a conversion step, which is mediated by cytochrome P450 enzymes. Based on in-vitro and in-vivo studies, it can be assumed that CYP3A, CYP2E and CYP2C are involved in the metabolism of levonorgestrel. Likewise, inducers or inhibitors of these enzymes may either, respectively, decrease the therapeutic effects or result in adverse reactions.

8 USE IN SPECIFIC POPULATIONS

8.1 Pregnancy

Risk Summary

Climara Pro is not indicated for use in pregnancy. There are no data with the use of Climara Pro in pregnant women; however, epidemiologic studies and meta-analyses have not found an increased risk of genital or nongenital birth defects (including cardiac anomalies and limb-reduction defects) following exposure to combined hormonal contraceptives (estrogens and progestins) before conception or during early pregnancy.

In the U.S. general population, the estimated background risk of major birth defects and miscarriage in clinically recognized pregnancies is 2% to 4% and 15% to 20%, respectively.

8.2 Lactation

Risk Summary

Estrogens plus progestogens are present in human milk and can reduce milk production in breast-feeding women. This reduction can occur at any time but is less likely to occur once breast-feeding is well-established. The developmental and health benefits of breastfeeding should be considered along with the mother’s clinical need for Climara Pro and any potential adverse effects on the breastfed child from Climara Pro or from the underlying maternal condition.

8.4 Pediatric Use

Climara Pro is not indicated for use in pediatric patients. Clinical studies have not been conducted in the pediatric population.

8.5 Geriatric Use

There have not been sufficient numbers of geriatric women involved in clinical studies utilizing Climara Pro to determine whether those over 65 years of age differ from younger subjects in their response to Climara Pro.

The Women’s Health Initiative Studies

In the WHI estrogen plus progestin substudy (daily CE [0.625 mg] plus MPA [2.5 mg] versus placebo), there was a higher relative risk of nonfatal stroke and invasive breast cancer in women greater than 65 years of age [see Clinical Studies (14.5)].

In the WHI estrogen-alone substudy (daily CE [0.625 mg]-alone versus placebo), there was a higher relative risk of stroke in women greater than 65 years of age [see Clinical Studies (14.5)]

The Women’s Health Initiative Memory Study

In the WHIMS ancillary studies of postmenopausal women 65 to 79 years of age, there was an increased risk of developing probable dementia in women receiving estrogen plus progestin or estrogen-alone when compared to placebo [see Warnings and Precautions (5.3), and Clinical Studies (14.6)].

Since both ancillary studies were conducted in women 65 to 79 years of age, it is unknown whether these findings apply to younger postmenopausal women^8 (see Warnings and Precautions (5.3), and Clinical Studies (14.6)].

10 OVERDOSAGE

Overdosage of estrogen plus progestogen may cause nausea, vomiting, breast tenderness, abdominal pain, drowsiness and fatigue, and withdrawal bleeding may occur in women. Treatment of overdose consists of discontinuation of Climara Pro therapy with institution of appropriate symptomatic care.

11 DESCRIPTION

Climara Pro (estradiol/levonorgestrel transdermal system) is an adhesive-based matrix transdermal patch designed to release both estradiol and levonorgestrel, a progestational agent, continuously upon application to intact skin. The 22 cm^2 Climara Pro system contains 4.4 mg estradiol and 1.39 mg levonorgestrel and provides a nominal delivery rate (mg per day) of 0.045 estradiol and 0.015 levonorgestrel.

Estradiol USP has a molecular weight of 272.39 and the molecular formula is C18H24O2.

Levonorgestrel USP has a molecular weight of 312.4 and a molecular formula of C21H28O2.

The structural formulas for estradiol and levonorgestrel are:

The Climara Pro transdermal system comprises 3 layers. Proceeding from the visible surface towards the surface attached to the skin, these layers are:

1. A translucent polyethylene backing film.
2. An acrylate adhesive matrix containing estradiol and levonorgestrel.
3. A protective liner of either siliconized or fluoropolymer coated polyester film. The protective liner is attached to the adhesive surface and must be removed before the system can be used.

The active components of the transdermal system are estradiol and levonorgestrel. The remaining components of the transdermal system (acrylate copolymer adhesive and polyvinylpyrrolidone/vinyl acetate copolymer) are pharmacologically inactive.

12 CLINICAL PHARMACOLOGY

12.1 Mechanism of Action

Endogenous estrogens are largely responsible for the development and maintenance of the female reproductive system and secondary sexual characteristics. Although circulating estrogens exist in a dynamic equilibrium of metabolic interconversions, estradiol is the principal intracellular human estrogen and is substantially more potent than its metabolites, estrone and estriol, at the receptor level.

The primary source of estrogen in normally cycling adult women is the ovarian follicle, which secretes 70 to 500 mcg of estradiol daily, depending on the phase of the menstrual cycle. After menopause, most endogenous estrogen is produced by conversion of androstenedione, which is secreted by the adrenal cortex, to estrone in the peripheral tissues. Thus, estrone and the sulfate conjugated form, estrone sulfate, are the most abundant circulating estrogens in postmenopausal women.

Estrogens act through binding to nuclear receptors in estrogen-responsive tissues. To date, two estrogen receptors have been identified. These vary in proportion from tissue to tissue.

Circulating estrogens modulate the pituitary secretion of the gonadotropins, luteinizing hormone (LH) and FSH, through a negative feedback mechanism. Estrogens act to reduce the elevated levels of these hormones seen in postmenopausal women.

Levonorgestrel inhibits gonadotropin production resulting in retardation of follicular growth and inhibition of ovulation.

Studies to assess the potency of progestins using estrogen-primed postmenopausal endometrial biochemistry and morphologic features have shown that levonorgestrel counteracts the proliferative effects of estrogens on the endometrium.

12.2 Pharmacodynamics

Generally, a serum estrogen concentration does not predict an individual woman’s therapeutic response to Climara nor her risk for adverse outcomes. Likewise, exposure comparisons across different estrogen products to infer efficacy or safety for the individual woman may not be valid.

12.3 Pharmacokinetics

Absorption

Transdermal administration of Climara Pro produces mean maximum estradiol concentrations in serum in about 2 to 2.5 days. Estradiol concentrations equivalent to the normal ranges observed at the early follicular phase in premenopausal women are achieved within 12–24 hours after the first application.

In one study, steady state estradiol concentrations in serum were measured during week 4 in 44 healthy, postmenopausal women during four consecutive Climara Pro applications of two formulations (0.045 mg estradiol/0.03 mg levonorgestrel and 0.045 mg estradiol/0.015 mg levonorgestrel) to the abdomen (each dose was applied for four 7-day periods). Both formulations were bioequivalent in terms of estradiol and estrone Cmax and AUC parameters. A summary of Climara Pro single and multiple applications estradiol, estrone and levonorgestrel pharmacokinetic parameters is shown in Table 2.

Table 2: Summary of Mean Pharmacokinetic Parameters
Summary of Mean (± SD) Pharmacokinetic Parameters Following a Single Application
of Climara Pro in 24 Healthy Postmenopausal Women
Parameter | Units | Estradiol | Estrone | Levonorgestrel
Single application Week 1 Data
Cave | Pg/mL | 37.7 ± 10.4 | 41 ± 15 | 136 ± 52.7
Cmax | Pg/mL | 54.3 ± 18.9 | 43.9 ± 14.9 | 138 ± 51.8
Tmax | Hours | 42 | 84 | 90
Cmin | Pg/mL | 27.2 ± 7.66 | 32.6 ± 14.3 | 110 ± 41.7
AUC | Pg.h/mL | 6340 ± 1740 | 6890 ± 2520 | 22900 ± 8860
Summary of Mean (± SD) Pharmacokinetic Parameters (Week 4) Following Four Consecutive Weekly Applications of Climara Pro in 44 Healthy Postmenopausal Women
Multiple application Week 4 Data
Cave | Pg/mL | 35.7 ± 11.4 | 45.5 ± 62.6 | 166 ± 97.8
Cmax | Pg/mL | 50.7 ± 28.6 | 81.6 ± 252 | 194 ± 111
Tmax | Hours | 36 | 48 | 48
Cmin | Pg/mL | 33.8 ± 28.7 | 72.5 ± 253 | 153 ± 69.6
AUC | Pg.h/mL | 6002 ± 1919 | 7642 ± 10518 | 27948 ± 16426

All mean parameters are arithmetic means except Tmax which is expressed as the median.

At steady state, Climara Pro maintains during the application period an average serum estradiol concentration of 35.7 pg/mL as depicted in Figure 1.

Figure 1: Mean Estradiol Concentration Profile (Week 4) Following Four Consecutive Weekly Applications of Climara Pro

Following the application of the Climara Pro transdermal system, levonorgestrel concentrations are maximum in about 2.5 days. At steady state, Climara Pro maintains during the application period an average serum levonorgestrel concentration of 166 pg/mL as depicted in Figure 2. The mean levonorgestrel pharmacokinetic parameters of Climara Pro are summarized in Table 2.

Figure 2: Mean Levonorgestrel Concentration Profile (Week 4) Following Four Consecutive Weekly Applications of Climara Pro

Adhesion

A study of the adhesion potential of Climara Pro was conducted in 104 healthy women of 45–75 years of age. Each woman applied a placebo patch, containing only the Climara Pro adhesive without active ingredient, to the upper outer abdominal areas weekly for three weeks. The adhesion assessment was done visually on Days 2, 4, 5, 6 and 7 of each of the three weeks using a four-point scale. The mean scores ranked in the highest category possible on the 0 to 4 scale demonstrating clinically acceptable adhesion performance

Excretion

Estradiol, estrone, and estriol are excreted in the urine along with glucuronide and sulfate conjugates. Following patch removal, serum estradiol concentrations decline with a mean (± SD) terminal half-life of 3± 0.67 hours.

Levonorgestrel and its metabolites are primarily excreted in the urine. Mean (± SD) terminal half-life for levonorgestrel was determined to be 28 ± 6.4 hours.

Metabolism

Exogenous estrogens are metabolized in the same manner as endogenous estrogens. Circulating estrogens exist in a dynamic equilibrium of metabolic interconversions. These transformations take place mainly in the liver. Estradiol is converted reversibly to estrone, and both can be converted to estriol, which is a major urinary metabolite. Estrogens also undergo enterohepatic recirculation via sulfate and glucuronide conjugation in the liver, biliary secretion of conjugates into the intestine, and hydrolysis in the intestine followed by reabsorption. In postmenopausal women, a significant proportion of the circulating estrogens exist as sulfate conjugates, especially estrone sulfate, which serves as a circulating reservoir for the formation of more active estrogens.

The most important metabolic pathway for levonorgestrel occurs in the reduction of the Δ4- and the 3-oxo-group as well as hydroxylations at positions 2α, 1β, and 16β, followed by conjugation. Most of the metabolites that circulate in the blood are sulfates of 3α, 5β-tetrahydro-levonorgestrel, while excretion occurs predominantly in the form of glucuronides. Some of the parent levonorgestrel also circulates as the 17β-sulfate. In-vitro studies on the biotransformation of levonorgestrel in human skin did not indicate any significant metabolism of levonorgestrel during skin penetration.

Distribution

The distribution of exogenous estrogens is similar to that of endogenous estrogens. Estrogens are widely distributed in the body and are generally found in higher concentrations in the sex hormone target organs. Estrogens circulate in the blood largely bound to SHBG and albumin.

Levonorgestrel in serum is bound to both SHBG and albumin. Following four consecutive weekly applications of Climara Pro mean (± SD) SHBG concentrations declined from a predose value of 47.5 (25.8) to 41.2 (22.4) nmol/L at week 4.

13 NONCLINICAL TOXICOLOGY

13.1 Carcinogenesis, Mutagenesis, Impairment of Fertility

Long-term continuous administration of natural and synthetic estrogens in certain animal species increases the frequency of carcinomas of the breast, uterus, cervix, vagina, testis, and liver.

14 CLINICAL STUDIES

14.1 Effects on Vasomotor Symptoms in Postmenopausal Women

The efficacy of 0.045 mg estradiol/0.03 mg levonorgestrel administered weekly versus placebo in the relief of moderate to severe vasomotor symptoms in postmenopausal women was studied in one 12-week clinical trial (n=183, average age 52.1 ± 4.93, 82 percent Caucasian). The 0.045 mg estradiol/0.03 mg levonorgestrel dosage strength was shown to be statistically better than placebo at weeks 4 and 12 for relief of both the number and severity of moderate to severe hot flushes. See Tables 3 and 4. Climara Pro and the 0.045 mg estradiol/0.03 mg levonorgestrel dosage strength are bioequivalent in terms of estradiol delivery [See Clinical Pharmacology (12.3)].

Table 3: Summary of Mean Daily Number of Moderate to Severe Hot Flushes-ITT [Intent-to-Treat population]
 |  | Baseline [A participating woman was included at baseline only if she had a post-baseline mean score. The post-baseline mean score required 3 days in one week.] | Week 4 | Week 8 | Week 12
Placebo | n [n = Number of participating women in a treatment group in a cycle; number of women varied from cycle to cycle due to missing data.] | 88 | 82 | 73 | 69
 | Mean (SD) [SD = standard deviation] | 10.8; (5.803) | 6.13; (4.311) | 5.35; (4.095) | 5.59; (4.93)
 | Mean Change; from baseline (SD) | NA | -4.23; (4.374) | -4.8; (4.448) | -4.55; (5.407)
0.045/.03 | n | 92 | 88 | 80 | 73
 | Mean (SD) | 10.13; (3.945) | 2.69; (4.455) | 1.22; (2.804) | 1.06; (3.187)
 | Mean Change; from baseline (SD) | NA | -7.4; (4.715) | -8.68; (4.146) | -8.82; (4.336)
p-Value [p-value for comparison to placebo, adjusted by the method of Bonferroni] |  | NA | <0.001 [p <0.025] | NA | <0.001

Table 4: Summary of Mean Severity of Moderate to Severe Hot Flushes-ITT [ITT= Intent-to-Treat population]
 |  | Baseline [A participating woman was included at baseline only if she had at least 1 post-baseline value.] | Week 4; (day 7) | Week 8; (day 7) | Week 12; (day 7)
Placebo | n | 89 | 76 | 68 | 57
 | Mean (SD)d | 2.42; (0.282) | 1.99; (0.875) | 1.93; (0.955) | 1.8; (1.034)
 | Mean Change; from baseline; (SD) [SD= standard deviation Severity scores are: 1 = Mild, 2 = Moderate, 3 = Severe. Mean severity of hot flushes by day is [(2X number of moderate hot flushes) + (3X number of severe hot flushes)] / total number of moderate to severe hot flushes on that day. If no moderate to severe hot flush was indicated, the mean severity was 0.] | NA | -0.4; (0.865) | -0.48; (0.922) | -0.57; (1.044)
0.045/.03 | n | 92 | 83 | 72 | 55
 | Mean (SD) | 2.48; (0.295) | 1.1; (1.191) | 0.82; (1.226) | 0.44; (0.96)
 | Mean Change; from baseline; (SD) | NA | -1.4; (1.164) | -1.67; (1.245) | -2.06; (1.005)
p-value [p-value for comparison to placebo, adjusted by the method of Bonferroni] |  | NA | <0.001 [p <0.025] | NA | <0.001

14.2 Effects on the Endometrium in Postmenopausal Women

In a 1-year clinical trial of 412 postmenopausal women (with intact uteri) treated with a continuous regimen of Climara Pro or with an continuous estradiol-only transdermal system, results of evaluable endometrial biopsies show that no hyperplasia was seen with Climara Pro. Table 5 below summarizes these results (Intent-to-Treat populations).

Table 5: Incidence of Endometrial Hyperplasia during Continuous Combined Treatment with Climara Pro, ITT [ITT = Intent-to-Treat population]
 | Climara Pro; E2 0.045 mg / LNG 0.015 mg | Estradiol; E2 0.045 mg
 | n [n = number of intent-to-treat in women.] = 210 | na = 202
No. of Patients with Biopsies at >6 months [Defined as at least 180 days of treatment.] | 124 | 139
No. of Patients with Biopsies at 1 year [Defined as ≥ 323 days of treatment.] | 102 | 110
No. (%) of Patients with Hyperplasia [Includes hyperplasia occurring at any time after initiation of treatment as a proportion of patients with biopsies at 1 year.] | 0 (0%) [p < 0.0167 p-value for comparison to unopposed estradiol dose using the Fisher Exact test. P-values were adjusted by the method of Bonferroni.] | 19 (17.3%)
95% Confidence Interval | 0-3.55% | 9.75–24.79%

14.3 Effects on Uterine Bleeding or Spotting in Postmenopausal Women

The effects of Climara Pro on uterine bleeding or spotting, as recorded using an interactive voice response system, were evaluated in one 12-month clinical trial. Results are shown in Figure 3.

Figure 3: Cumulative Proportion of Subjects at Each Cycle with No Bleeding/Spotting Through the End of Cycle 13 Last Observation Carried Forward

- Percent based upon the number of participating women with data
- Last non-missing cycle carried forward through cycle 13
- Bleeding associated with endometrial biopsies not included

14.4 Effects on Bone Mineral Density in Postmenopausal Women

The effects on bone mineral density (BMD) were studied in a randomized, double-blind, placebo-controlled clinical trial of transdermal systems (patches) containing only estradiol (E2). Participants were postmenopausal women with hysterectomies, 40–83 years of age (mean=51.4 years), and 77.3 percent Caucasian. Women received calcium supplements if they appeared deficient on a questionnaire. Vitamin D supplements were not given.

A total of 154 women were randomized in a 2:2:3 ratio to weekly application of 22 cm^2 patches containing 2.2 mg E2, 4.4 mg E2, or placebo, for 728 days of continuous treatment (26 28-day cycles). Only the results for the estradiol dose in Climara Pro (4.4 mg E2) and for placebo are presented.

Statistically significant increases in the primary efficacy variable, BMD of the lumbar spine (A-P view, L2-L4), were seen for 4.4 mg E2 compared to placebo (see Table 5 and Figure 4). BMD was also measured at the hip (total, non-dominant side) and radius (midshaft, non-dominant side) with statistically significant treatment effects only observed for the hip (see Table 6).

Table 6: Mean Bone Mineral Density (Standard Deviation) [Intent-to-treat population with on-treatment efficacy data]
 | 4.4 mg E2 [E2=estradiol; LOCF= Last Observation Carried Forward] | Placebo
Total Lumbar Spine; Baseline (g/cm^2) | n=36; 1.1 (0.2) | n=46; 1.1 (0.2)
% Change from baseline LOCF | +1.7% (4.4) | -2.9% (3.8)
P-value compared to placebo | <0.0001
Total Hip; Baseline (g/cm^2) | n=36; 0.97 (0.1) | n=48; 0.94 (0.1)
% Change from baseline LOCF | +1.3% (4.2) | -0.9% (5.2)
P-value compared to placebo | 0.05

Figure 4: Percent Change From Baseline in Bone Mineral Density (g/cm2) of Lumbar Spine (A-P View, L2–L4) by Treatment Group and Cycle (Mean ± SE)*

* Data in the figure is for 21 patients on 4.4 mg E2 and 27 placebo patients who completed the study; approximately 44 percent of randomized patients.

14.5 Women's Health Initiative Studies

The WHI enrolled approximately 27,000 predominantly healthy postmenopausal women in two substudies to assess the risks and benefits of daily oral CE (0.625 mg)-alone or in combination with MPA (2.5 mg) compared to placebo in the prevention of certain chronic diseases. The primary endpoint was the incidence of CHD (defined as nonfatal MI, silent MI and CHD death), with invasive breast cancer as the primary adverse outcome. A "global index" included the earliest occurrence of CHD, invasive breast cancer, stroke, PE, endometrial cancer (only in the CE plus MPA substudy), colorectal cancer, hip fracture, or death due to other cause. These substudies did not evaluate the effects of CE plus MPA or CE-alone on menopausal symptoms.

WHI Estrogen Plus Progestin Substudy

The WHI estrogen plus progestin substudy was stopped early. According to the predefined stopping rule, after an average follow-up of 5.6 years of treatment, the increased risk of invasive breast cancer and cardiovascular events exceeded the specified benefits included in the "global index". The absolute excess risk of events included in the “global index” was 19 per 10,000 women-years.

For those outcomes included in the WHI “global index” that reached statistical significance after 5.6 years of follow-up, the absolute excess risks per 10,000 women-years in the group treated with CE plus MPA were 7 more CHD events, 8 more strokes, 10 more PEs, and 8 more invasive breast cancers, while the absolute risk reductions per 10,000 women-years were 6 fewer colorectal cancers and 5 fewer hip fractures.

Results of the CE plus MPA substudy, which included 16,608 women (average 63 years of age, range 50 to 79; 83.9 percent White, 6.8 percent Black, 5.4 percent Hispanic, 3.9 percent Other) are presented in Table 7. These results reflect centrally adjudicated data after an average follow-up of 5.6 years.

Table 7: Relative and Absolute Risk Seen in the Estrogen Plus Progestin Substudy of WHI at an Average of 5.6 Years [Adapted from numerous WHI publications. WHI publications can be viewed at www.nhlbi.nih.gov/whi.] [Results are based on centrally adjudicated data.]
Event | Relative Risk CE/MPA vs. Placebo (95% nCI [Nominal confidence intervals unadjusted for multiple looks and multiple comparisons]) | CE/MPA n = 8,506 | Placebo; n = 8,102
Event | Relative Risk CE/MPA vs. Placebo (95% nCI [Nominal confidence intervals unadjusted for multiple looks and multiple comparisons]) | Absolute Risk per 10,000 Women-Years
CHD events Non-fatal MI CHD death | 1.23 (0.99-1.53) 1.28 (1.00-1.63) 1.10 (0.70-1.75) | 41 | 34
CHD events Non-fatal MI CHD death | 1.23 (0.99-1.53) 1.28 (1.00-1.63) 1.10 (0.70-1.75) | 31 | 25
CHD events Non-fatal MI CHD death | 1.23 (0.99-1.53) 1.28 (1.00-1.63) 1.10 (0.70-1.75) | 8 | 8
All strokes | 1.31 (1.03-1.68) | 33 | 25
Ischemic stroke | 1.44 (1.09-1.90) | 26 | 18
Deep vein thrombosis [Not included in “global index.”] | 1.95 (1.43-2.67) | 26 | 13
Pulmonary embolism | 2.13 (1.45-3.11) | 18 | 8
Invasive breast cancer [Includes metastatic and non-metastatic breast cancer, with the exception of in situ breast cancer.] | 1.24 (1.01-1.54) | 41 | 33
Colorectal cancer | 0.61 (0.42-0.87) | 10 | 16
Endometrial cancer | 0.81 (0.48-1.36) | 6 | 7
Cervical cancer | 1.44 (0.47-4.42) | 2 | 1
Hip fracture | 0.67 (0.47-0.96) | 11 | 16
Vertebral fractures | 0.65 (0.46-0.92) | 11 | 17
Lower arm/wrist fractures | 0.71 (0.59-0.85) | 44 | 62
Total fractures | 0.76 (0.69-0.83) | 152 | 199
Overall Mortality [All deaths, except from breast or colorectal cancer, definite or probable CHD, PE or cerebrovascular disease.] | 1.00 (0.83-1.19) | 52 | 52
Global Index [A subset of the events was combined in a "global index", defined as the earliest occurrence of CHD events, invasive breast cancer, stroke, pulmonary embolism, colorectal cancer, hip fracture, or death due to other causes.] | 1.13 (1.02-1.25) | 184 | 165

Timing of the initiation of estrogen-alone therapy relative to the start of menopause may affect the overall risk benefit profile. The WHI estrogen-alone substudy, stratified by age, showed in women 50 to 59 years of age, a non-significant trend toward reduced risk for overall mortality [hazard ratio (HR) 0.69 (95 percent CI, 0.44–1.07)].

WHI Estrogen-Alone Substudy

The WHI estrogen-alone substudy was stopped early because an increased risk of stroke was observed, and it was deemed that no further information would be obtained regarding the risks and benefits of estrogen-alone in predetermined primary endpoints.

Results of the estrogen-alone substudy, which included 10,739 women (average age of 63 years, range 50 to 79; 75.3 percent White, 15.1 percent Black, 6.1 percent Hispanic, 3.6 percent Other), after an average follow-up of 7.1 years are presented in Table 8.

Table 8: Relative and Absolute Risk Seen in the Estrogen-Alone Substudy of WHI
Event | Relative Risk CE vs. Placebo (95% nCI [Nominal confidence intervals unadjusted for multiple looks and multiple comparisons.]) | CE n = 5,310 | Placebo n = 5,429
Event | Relative Risk CE vs. Placebo (95% nCI [Nominal confidence intervals unadjusted for multiple looks and multiple comparisons.]) | Absolute Risk per 10,000 Women-Years
CHD events [Results are based on centrally adjudicated data for an average follow-up of 7.1 years.] | 0.95 (0.78-1.16) | 54 | 57
Non-fatal MI | 0.91 (0.73-1.14) | 40 | 43
CHD death | 1.01 (0.71-1.43) | 16 | 16
All strokes | 1.33 (1.05-1.68) | 45 | 33
Ischemic stroke | 1.55 (1.19-2.01) | 38 | 25
Deep vein thrombosis, [Not included in “global index”.] | 1.47 (1.06-2.06) | 23 | 15
Pulmonary embolism | 1.37 (0.90-2.07) | 14 | 10
Invasive breast cancer | 0.80 (0.62-1.04) | 28 | 34
Colorectal cancer | 1.08 (0.75-1.55) | 17 | 16
Hip fracture | 0.65 (0.45-0.94) | 12 | 19
Vertebral fractures, | 0.64 (0.44-0.93) | 11 | 18
Lower arm/wrist fractures, | 0.58 (0.47-0.72) | 35 | 59
Total fractures, | 0.71 (0.64-0.80) | 144 | 197
Death due to other causes [Results are based on an average follow-up of 6.8 years.] , [All deaths, except from breast or colorectal cancer, definite/probable CHD, PE or cerebrovascular disease.] | 1.08 (0.88-1.32) | 53 | 50
Overall Mortality, | 1.04 (0.88-1.22) | 79 | 75
Global Index [A subset of the events was combined in a "global index", defined as the earliest occurrence of CHD events, invasive breast cancer, stroke, pulmonary embolism, colorectal cancer, hip fracture, or death due to other causes.] | 1.02 (0.92-1.13) | 206 | 201

For those outcomes included in the WHI "global index" that reached statistical significance, the absolute excess risk per 10,000 women-years in the group treated with CE- alone was 12 more strokes, while the absolute risk reduction per 10,000 women-years was 7 fewer hip fractures.^9 The absolute excess risk of events included in the "global index" was a non-significant 5 events per 10,000 women-years. There was no difference between the groups in terms of all-cause mortality.

No overall difference for primary CHD events (nonfatal MI, silent MI and CHD death) and invasive breast cancer incidence in women receiving CE-alone compared with placebo was reported in final centrally adjudicated results from the estrogen-alone substudy, after an average follow-up of 7.1 years.

Centrally adjudicated results for stroke events from the estrogen-alone substudy, after an average follow-up of 7.1 years, reported no significant difference in distribution of stroke subtype or severity, including fatal strokes, in women receiving CE-alone compared to placebo. Estrogen-alone increased the risk for ischemic stroke, and this excess risk was present in all subgroups of women examined.^10

Timing of the initiation of estrogen-alone therapy relative to the start of menopause may affect the overall risk benefit profile. The WHI estrogen-alone substudy stratified by age showed in women 50 to 59 years of age, a non-significant trend toward reduced risk for CHD [HR 0.63 (95 percent CI, 0.36-1.09)] and overall mortality [HR 0.71 (95 percent CI, 0.46-1.11)].

14.6 Women's Health Initiative Memory Study

The WHIMS estrogen plus progestin ancillary study of WHI enrolled 4,532 predominantly healthy postmenopausal women 65 to 79 years of age and older (47 percent were 65 to 69 years of age, 35 percent were 70 to 74 years of age, and 18 percent were 75 years of age and older) to evaluate the effects of daily CE (0.625 mg) plus MPA (2.5 mg) on the incidence of probable dementia (primary outcome) compared to placebo.

After an average follow-up of 4 years, the relative risk of probable dementia for CE plus MPA versus placebo was 2.05 (95 percent CI, 1.21-3.48). The absolute risk of probable dementia for CE plus MPA was 45 versus 22 cases per 10,000 women-years. Probable dementia as defined in this study included Alzheimer’s disease (AD), vascular dementia (VaD) and mixed type (having features of both AD and VaD). The most common classification of probable dementia in the treatment group and the placebo group was AD. Since the ancillary study was conducted in women 65 to 79 years of age, it is unknown whether these findings apply to younger postmenopausal women [see Warnings and Precautions (5.3), and Use in Specific Populations (8.5)].

The WHIMS estrogen-alone ancillary study of WHI enrolled 2,947 predominantly healthy hysterectomized postmenopausal women 65 years of age and older (45 percent were age 65 to 69 years of age, 36 percent were 70 to 74 years of age, and 19 percent were 75 years of age and older) to evaluate the effects of daily CE (0.625 mg)-alone on the incidence of probable dementia (primary outcome) compared to placebo.

After an average follow-up of 5.2 years, the relative risk of probable dementia for CE-alone versus placebo was 1.49 (95 percent CI, 0.83-2.66). The absolute risk of probable dementia for CE-alone versus placebo was 37 versus 25 cases per 10,000 women-years. Probable dementia as defined in this study included Alzheimer’s disease (AD), vascular dementia (VaD) and mixed type (having features of both AD and VaD). The most common classification of probable dementia in the treatment group and the placebo groups was AD. Since the ancillary study was conducted in women 65 to 79 years of age, it is unknown whether these findings apply to younger postmenopausal women [see Warnings and Precautions (5.3), and Use in Specific Populations (8.5)].

When data from the two populations were pooled as planned in the WHIMS protocol, the reported overall relative risk for probable dementia was 1.76 (95 percent CI, 1.19-2.60). Differences between groups became apparent in the first year of treatment. It is unknown whether these findings apply to younger postmenopausal women [see Warnings and Precautions (5.3), and Use in Specific Populations (8.5)].

15 REFERENCES

- Rossouw JE, et al. Postmenopausal Hormone Therapy and Risk of Cardiovascular Disease by Age and Years Since Menopause. JAMA. 2007;297:1465-1477.
- Hsia J, et al. Conjugated Equine Estrogens and Coronary Heart Disease. Arch Int Med. 2006;166:357-365.
- Cushman M, et al. Estrogen Plus Progestin and Risk of Venous Thrombosis. JAMA. 2004;292:1573-1580.
- Curb JD, et al. Venous Thrombosis and Conjugated Equine Estrogen in Women Without a Uterus. Arch Int Med. 2006;166:772-780.
- Chlebowski RT, et al. Influence of Estrogen Plus Progestin on Breast Cancer and Mammography in Healthy Postmenopausal Women. JAMA. 2003;289:3234-3253.
- Stefanick ML, et al. Effects of Conjugated Equine Estrogens on Breast Cancer and Mammography Screening in Postmenopausal Women With Hysterectomy. JAMA. 2006;295:1647-1657.
- Anderson GL, et al. Effects of Estrogen Plus Progestin on Gynecologic Cancers and Associated Diagnostic Procedures. JAMA. 2003;290:1739-1748.
- Shumaker SA, et al. Conjugated Equine Estrogens and Incidence of Probable Dementia and Mild Cognitive Impairment in Postmenopausal Women. JAMA. 2004;291:2947-2958.
- Jackson RD, et al. Effects of Conjugated Equine Estrogen on Risk of Fractures and BMD in Postmenopausal Women With Hysterectomy: Results From the Women's Health Initiative Randomized Trial. J Bone Miner Res. 2006;21:817-828.
- Hendrix SL, et al. Effects of Conjugated Equine Estrogen on Stroke in the Women's Health Initiative. Circulation. 2006;113:2425-2434.

16 HOW SUPPLIED/STORAGE AND HANDLING

16.1 How Supplied

Individual Carton of 4 systems

Climara Pro (estradiol/levonorgestrel transdermal system) 0.045 mg/day estradiol and 0.015 mg/day levonorgestrel – each 22 cm^2 system contains 4.4 mg of estradiol and 1.39 mg of levonorgestrel. NDC 50419-491-04

16.2 Storage and Handling

Store at 20°C to 25°C (68°F to 77°F); excursions permitted to 15°C to 30°C (59°F to 86°F) [see USP controlled Room Temperature].

Do not store unpouched. Apply immediately upon removal from the protective pouch.

Used transdermal systems still contain active hormones. To discard, fold the sticky side of the transdermal system together, place it in a sturdy child-proof container, and place this container in the trash. Used transdermal systems should not be flushed in the toilet

17 PATIENT COUNSELING INFORMATION

Advise women to read the FDA-approved patient labeling (Patient Information and Instructions for Use)

Vaginal Bleeding

Inform postmenopausal women to report any vaginal bleeding to their healthcare provider as soon as possible [see Warning and Precautions (5.2)].

Possible Serious Adverse Reactions with Estrogen Plus Progestogen Therapy

Inform postmenopausal women of possible serious adverse reactions of estrogen plus progestogen therapy including Cardiovascular Disorders, Malignant Neoplasms, and Probable Dementia [see Warning and Precautions (5.1, 5.2, 5.3)].

Possible Common Adverse Reactions with Estrogen plus Progestogen Therapy

Inform postmenopausal women of possible less serious but common adverse reactions of estrogen plus progestogen therapy such as headache, breast pain and tenderness, nausea and vomiting.

Patient Package Insert

Patient Information

Climara Pro (Klī-mâr-uh prō)

(estradiol/levonorgestrel transdermal system)

Read this Patient Information before you start using Climara Pro and each time you get a refill. There may be new information. This information does not take the place of talking to your healthcare provider about your menopausal symptoms or your treatment.

What is the most important information I should know about Climara Pro (a combination of estrogen and progestogen)?

- Do not use estrogens with or without progestogens to prevent heart disease, heart attacks, strokes, or dementia (declines of brain function).
- Using estrogens with progestogens may increase your chances of getting heart attacks, strokes, breast cancer, or blood clots.
- Using estrogens with progestogens may increase your chance of getting dementia, based on a study of women 65 years of age and older.
- Using estrogen-alone may increase your chance of getting cancer of the uterus (womb).
- Do not use estrogen-alone to prevent heart disease, heart attacks, strokes or dementia.

- Using estrogen-alone may increase your chances of getting strokes or blood clots.
- Using estrogen-alone may increase your chance of getting dementia, based on a study of women 65 years of age and older.
- Only one estrogen with progestogen product and dose have been shown to increase your chances of getting heart attacks, strokes, breast cancer, blood clots, and dementia. Only one estrogen-alone product and dose have been shown to increase your chances of getting strokes, blood clots, and dementia.
Because other products and doses have not been studied in the same way, it is not known how the use of Climara Pro will affect your chances of these conditions. You and your healthcare provider should talk regularly about whether you still need treatment with Climara Pro.

What is Climara Pro?

Climara Pro is a prescription medicine patch (transdermal system) that contains two kinds of hormones, an estrogen and a progestogen.

What is Climara Pro used for?

Climara Pro is used after menopause to:

- Reduce moderate to severe hot flashes
Estrogens are hormones made by a woman's ovaries. The ovaries normally stop making estrogens when a woman is between 45 and 55 years old. This drop in body estrogen levels causes the "change of life" or menopause (the end of monthly menstrual periods). Sometimes, both ovaries are removed during an operation before natural menopause takes place. The sudden drop in estrogen levels causes "surgical menopause."
When the estrogen levels begin dropping, some women get very uncomfortable symptoms, such as feelings of warmth in the face, neck, and chest, or sudden intense feelings of heat and sweating ("hot flashes" or "hot flushes"). In some women, the symptoms are mild, and they will not need to use estrogens. In other women, symptoms can be more severe.
- Help reduce your chances of getting osteoporosis (thin weak bones)
Osteoporosis from menopause is a thinning of the bones that makes them weaker and easier to break. If you use Climara Pro to prevent osteoporosis from menopause, talk with your healthcare provider about whether a different treatment or medicine without estrogens might be better for you.
You and your healthcare provider should talk regularly about whether you still need treatment with Climara Pro.

Who should not use Climara Pro?

Do not use Climara Pro if you have had your uterus (womb) removed (hysterectomy).

Climara Pro contains a progestogen to decrease the chance of getting cancer of the uterus. If you do not have a uterus, you do not need a progestogen and you should not use Climara Pro.

Do not start using Climara Pro if you:

- have any unusual vaginal bleeding
Vaginal bleeding after menopause may be a warning sign of cancer of the uterus (womb). Your healthcare provider should check any unusual vaginal bleeding to find out the cause.
- have been diagnosed with a bleeding disorder
- currently have or have had certain cancers
Estrogens may increase the chance of getting certain types of cancers, including cancer of the breast or uterus (womb). If you have or have had cancer, talk with your healthcare provider about whether you should use Climara Pro.
- had a stroke or heart attack
- currently have or have had blood clots
- currently have or have had liver problems
- are allergic to Climara Pro or any of the ingredients in it.
See the list of ingredients in Climara Pro at the end of this leaflet.

Before you use Climara Pro, tell your healthcare provider about all of your medical conditions, including if you:

- have any unusual vaginal bleeding
Vaginal bleeding after menopause may be a warning sign of cancer of the uterus (womb). Your healthcare provider should check any unusual vaginal bleeding to find out the cause.
- have any other medical conditions that may become worse while you are using Climara
Your healthcare provider may need to check you more carefully if you have certain conditions, such as asthma (wheezing), epilepsy (seizures), diabetes, migraine, endometriosis, lupus, angioedema (swelling of face and tongue), or problems with your heart, liver, thyroid, kidneys, or have high calcium levels in your blood.
- are going to have surgery or will be on bed rest
Your healthcare provider will let you know if you need to stop using Climara Pro.

- are pregnant or think you may be pregnant.
Climara is not for pregnant women.
- are breastfeeding
The hormones in Climara Pro can pass into your breast milk.

Tell your healthcare provider about all the medicines you take, including prescription and over-the-counter medicines, vitamins, and herbal supplements. Some medicines may affect how Climara Pro works. Climara Pro may also affect how your other medicines work. Keep a list of your medicines and show it to your healthcare provider and pharmacist when you get a new medicine.

How should I use Climara Pro?

For detailed instructions, see the step-by-step instructions for using Climara Pro at the end of this Patient Information.

- Use Climara Pro exactly as your healthcare provider tells you to use it.
- Climara Pro is for skin use only.
- Change your Climara Pro patch 1 time each week or every 7 days.
- Apply your Climara Pro patch to a clean, dry area on your lower abdomen or buttocks. This area must be clean, dry, and free of powder, oil or lotion for your patch to stick to your skin.
- Apply your Climara Pro patch to a different area of your abdomen or your buttocks each time. Do not use the same application site 2 times in the same week.
- Do not apply Climara Pro to your breasts.
- If you forget to apply a new Climara Pro, apply a new patch as soon as possible.
- You and your healthcare provider should talk regularly (every 3 to 6 months) about the dose you are using and whether you still need treatment with Climara Pro.

How do I change Climara Pro?

- When changing Climara Pro, peel off the used patch slowly from the skin.
- After removal of Climara Pro, if any adhesive residue remains on your skin after removing the patch, allow the area to dry for 15 minutes. Then, gently rub the area with an oil-based cream or lotion to remove the adhesive from your skin.
- Apply the new patch to a different skin area of your lower abdomen or buttocks. This area must be clean, dry, and free of powder, oil or lotion. Do not use the same site again for at least 1 week after removal of the patch.

What are the possible side effects of Climara Pro?

Side effects are grouped by how serious they are and how often they happen when you are treated.

Serious, but less common side effects include:

- heart attack
- stroke
- blood clots
- breast cancer
- cancer of the lining of the uterus (womb)
- cancer of the ovary
- dementia
- high or low blood calcium
- gallbladder disease
- visual abnormalities
- high blood pressure
- cancer changes of endometriosis
- high levels of fat (triglyceride) in your blood
- liver problems
- changes in your thyroid hormone levels
- fluid retention
- enlargement of benign tumors of the uterus (“fibroids”)
- worsening of swelling of face and tongue (angioedema) in women with a history of angioedema

Call your healthcare provider right away if you get any of the following warning signs or any other unusual symptoms that concern you:

- new breast lumps
- unusual vaginal bleeding
- changes in vision or speech
- sudden new severe headaches
- severe pains in your chest or legs with or without shortness of breath, weakness and fatigue

Common side effects of Climara Pro include:

These are not all the possible side effects of Climara Pro. For more information, ask your healthcare provider or pharmacist. Tell your healthcare provider if you have any side effects that bother you or do not go away.

You may report side effects to FDA at 1-800-FDA-1088. You may also report side effects to Bayer Healthcare Pharmaceuticals at 1-888-842-2937.

What can I do to lower my chances of a serious side effect with Climara Pro?

- Talk with your healthcare provider regularly about whether you should continue using Climara Pro.
- If you have a uterus, talk with your healthcare provider about whether Climara Pro is right for you. In general, the addition of a progestogen is generally recommended for a woman with a uterus to reduce the chance of getting cancer of the uterus (womb).
- See your healthcare provider right away if you get vaginal bleeding while using Climara Pro.
- Have a pelvic exam, breast exam and mammogram (breast X-ray) every year unless your healthcare provider tells you something else. If members of your family have had breast cancer or if you have ever had breast lumps or an abnormal mammogram, you may need to have breast exams more often.
- If you have high blood pressure, high cholesterol (fat in the blood), diabetes, are overweight, or if you use tobacco, you may have higher chances for getting heart disease. Ask your healthcare provider for ways to lower your chances of getting heart disease.

How should I store and throw away used Climara Pro?

- Store at room temperature between 68°F to 77°F (20°C to 25°C).
- Do not store Climara Pro patches outside of their pouches. Apply immediately after removal from the protective pouch.
- Used patches still contain estrogen. To throw away the patch, fold the sticky side of the patch together, place it in a sturdy child-proof container, and place this container in the trash. Used patches should not be flushed in the toilet.

KEEP CLIMARA PRO and all medicines out of the reach of children.

General information about the safe and effective use of Climara Pro.

Medicines are sometimes prescribed for purposes other than those listed in Patient Information leaflets. Do not use Climara Pro for conditions for which it was not prescribed. Do not give Climara Pro to other people, even if they have the same symptoms you have. It may harm them.

You can ask your healthcare provider or pharmacist for information about Climara Pro that is written for health professionals. For more information, go to www.climara-us.com or call Bayer HealthCare Pharmaceuticals Inc. at 1-888-842-2937.

What are the ingredients in Climara Pro?

Active ingredient: estradiol and levonorgestrel

Inactive ingredient: acrylate copolymer adhesive, and polyvinylpyrrolidone/vinyl acetate copolymer.

Instructions for Use

Climara Pro (Klī-mâr-uh prō)

(estradiol transdermal system)

Read this Patient Information before you start using Climara Pro and each time you get a refill. There may be new information. This information does not take the place of talking to your healthcare provider about your menopausal symptoms or your treatment.

You will need the following supplies: See Figure A

Figure A

Step 1: Pick the days you will change your Climara Pro.

- You will need to change your patch 1 time each week or every 7 days.

Step 2. Remove the Climara Pro patch from the pouch.

- Remove patch from its protective pouch by tearing at the notch (do not use scissors). See Figure B
- Do not remove your patch from the protective pouch until you are ready to apply it.

Figure B

Step 3. Remove the adhesive liner. See Figure C

- You will see that Climara Pro is an oval shaped clear patch that is attached to a thick, hard-plastic adhesive liner and covered by a clear, plastic film. See Figure C
- To apply your patch you must first remove the protective, clear plastic film that is attached to the clear thicker plastic backing. See Figure D

Figure C

Figure D

Step 4. Placing the patch on your skin.

- Apply the sticky side of the patch to one of the areas of skin shown below. See Figure E and Figure F
- Do not touch the sticky side of the patch with your fingers.

Figure E

Figure F

Note:

- Avoid the waistline, since clothing and belts may cause the patch to be rubbed off.
- Do not apply Climara Pro to your breasts.
- Only apply Climara Pro to skin that is clean, dry, and free of any powder, oil, or lotion.
- You should not apply the patch to injured, burned, or irritated skin, or areas with skin conditions (such as birth marks, tattoos, or that is very hairy).

Step 5. Press the patch firmly onto your skin.

- Press the patch firmly in place with your fingers for at least 10 seconds
- Rub the edges of the patch to make sure that it will stick to your skin. (See Figure H)

Figure G

Note:

- Contact with water while you are swimming, using a sauna, bathing, or showering may cause the patch to fall off.
- If your patch falls off reapply it. If you cannot reapply the patch, apply a new patch to another area (See Figures E and F) and continue to follow your original application schedule.
- If you stop using your Climara Pro or forget to apply a new patch as scheduled, you may have spotting, or bleeding, and your symptoms may come back.

Step 6: Throwing away your used patch.

- When it is time to change your patch, remove the old patch before you apply a new patch.
- To throw away the patch, fold the sticky side of the patch together, place it in a sturdy child-proof container, and place this container in the trash. Do not flush used patches in the toilet.

This Patient Information and Instructions for Use have been approved by the U.S Food and Drug Administration.

© 2013, Bayer HealthCare Pharmaceuticals Inc. All rights reserved.

11/2021

Manufactured for:
Bayer HealthCare Pharmaceuticals Inc.
Whippany, NJ 07981